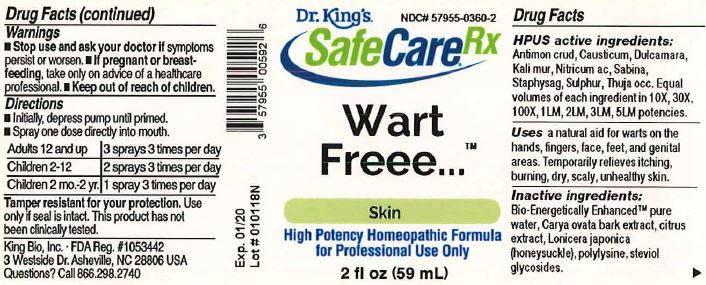 DRUG LABEL: Wart Freee
NDC: 57955-0360 | Form: LIQUID
Manufacturer: King Bio Inc.
Category: homeopathic | Type: HUMAN OTC DRUG LABEL
Date: 20180405

ACTIVE INGREDIENTS: ANTIMONY TRISULFIDE 10 [hp_X]/59 mL; CAUSTICUM 10 [hp_X]/59 mL; SOLANUM DULCAMARA TOP 10 [hp_X]/59 mL; POTASSIUM CHLORIDE 10 [hp_X]/59 mL; NITRIC ACID 10 [hp_X]/59 mL; JUNIPERUS SABINA LEAFY TWIG 10 [hp_X]/59 mL; DELPHINIUM STAPHISAGRIA SEED 10 [hp_X]/59 mL; SULFUR 10 [hp_X]/59 mL; THUJA OCCIDENTALIS LEAFY TWIG 10 [hp_X]/59 mL
INACTIVE INGREDIENTS: WATER; CARYA OVATA BARK; CITRUS BIOFLAVONOIDS; LONICERA JAPONICA FLOWER; POLYEPSILON-LYSINE (4000 MW); REBAUDIOSIDE A

Wart Freee™

ACTIVE INGREDIENT

Drug Facts__________________________________________________________________________________________________________

HPUS active ingredients: Antimon crud, Causticum, Dulcamara, Kali mur, Nitricum ac, Sabina, Staphysag, Sulphur, Thuja occ.

Equal volumes of each ingredient in 10X, 30X, 100X, 1LM, 2LM, 3LM, 5LM potencies.

INDICATIONS AND USAGE

Uses a natural aid for warts on the hands, fingers, face, feet and genital areas. Temporarily relieves itching, burning, dry, scaly, unhealthy skin.

Inactive Ingredients:

Bio-Energetically Enhanced™ pure water, Carya ovata bak extract, citrus extract, Lonicera japonica (honeysuckle), polylysine, steviol glycosides.

Warnings

- Stop use and ask your doctor if symptoms persist or worsen.
- If pregnant or breast-feeding, take only on advice of a healthcare professional.

- Keep out of reach of children.

Directions

- Initially, depress pump until primed.
- Spray one dose directly into mouth.
- Adults 12 and up: 3 sprays 3 times per day
- Children 2-12: 2 sprays 3 times per day
- Children 2 mo.-2 yr: 1 spray 3 times per day.

OTHER SAFETY INFORMATION

Tamper resistant for your protection. Use only if safety seal is intact. This product has not been clinically tested.

PURPOSE

Uses a natural aid for warts on the hands, fingers, face, feet and genital areas.

Temporarily relieves:

- itching
- burning
- dry
- scaly
- unhealthy skin